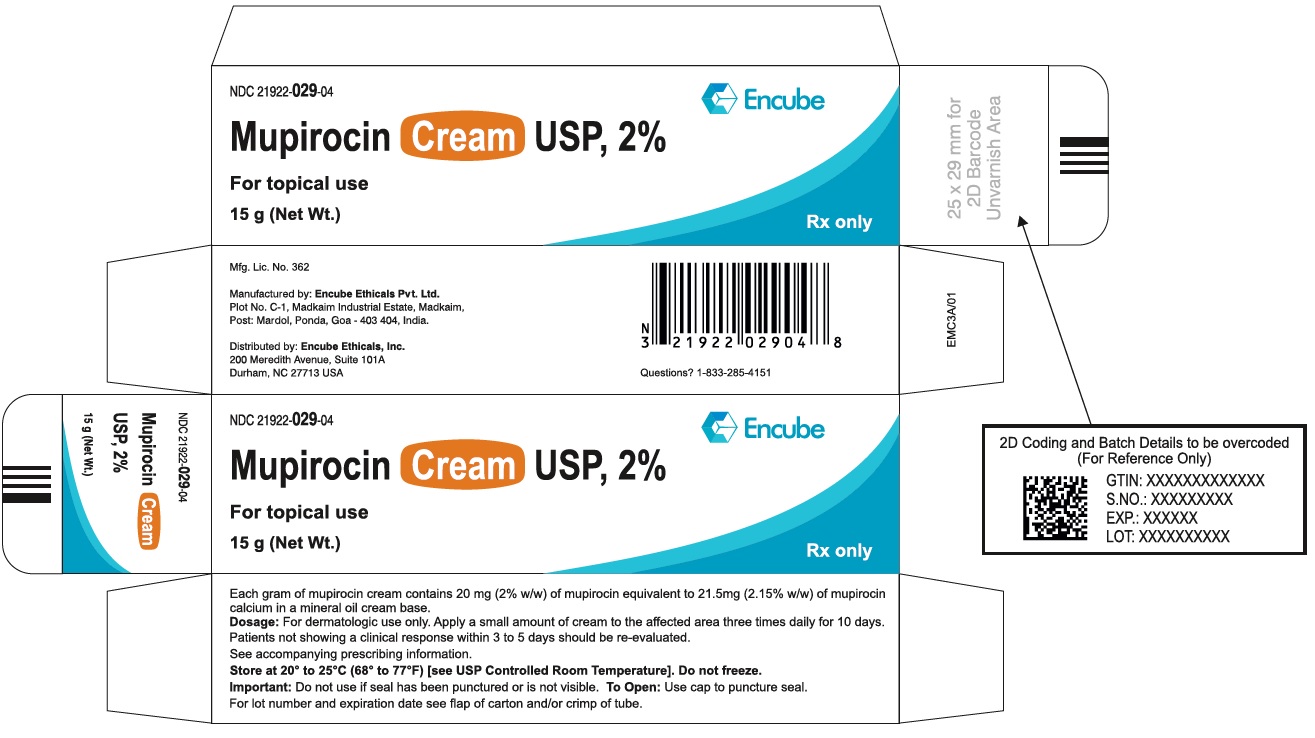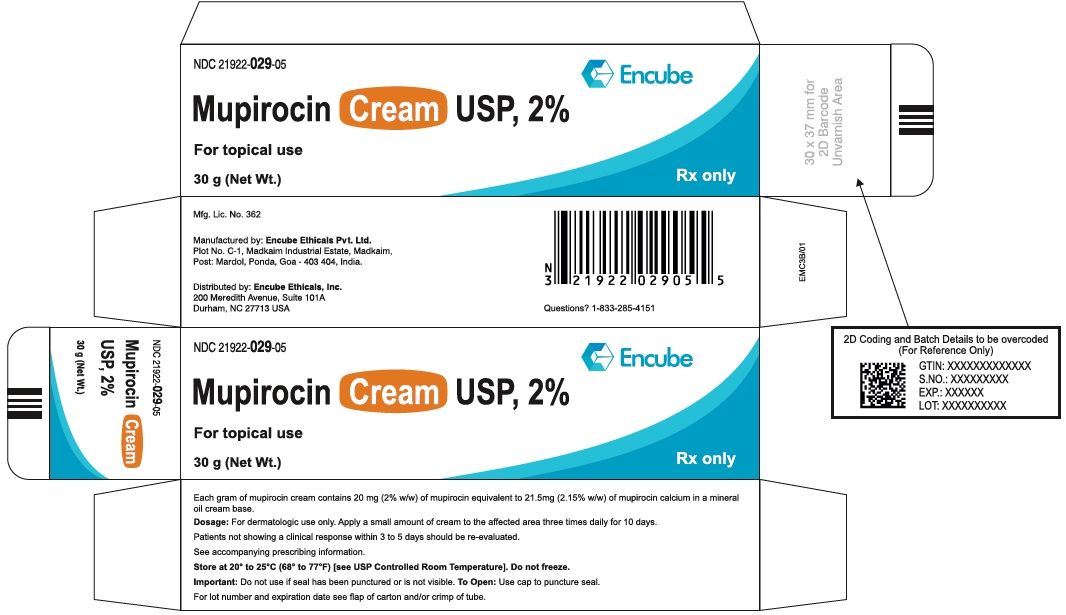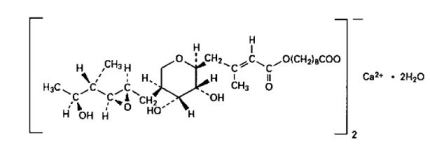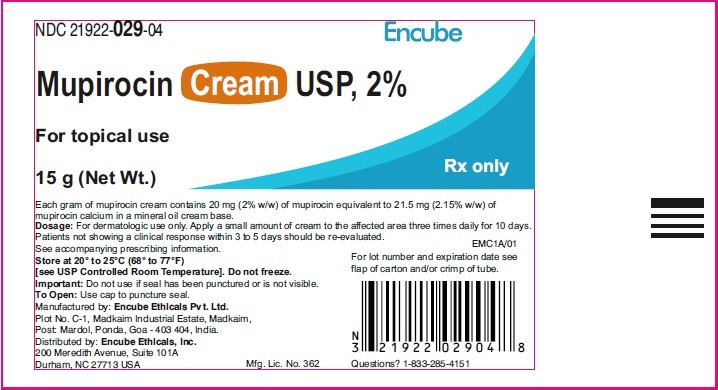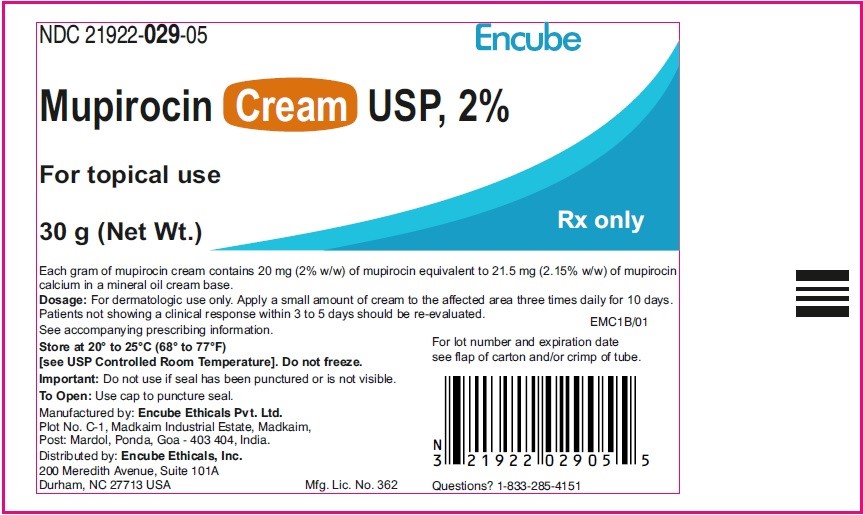 DRUG LABEL: Mupirocin
NDC: 21922-029 | Form: CREAM
Manufacturer: Encube Ethicals, Inc.
Category: prescription | Type: HUMAN PRESCRIPTION DRUG LABEL
Date: 20250926

ACTIVE INGREDIENTS: MUPIROCIN CALCIUM 2 g/100 g
INACTIVE INGREDIENTS: BENZYL ALCOHOL; POLYOXYL 20 CETOSTEARYL ETHER; GLYCERYL MONO AND DIPALMITOSTEARATE; MINERAL OIL; PHENOXYETHANOL; WATER; XANTHAN GUM

HIGHLIGHTS OF PRESCRIBING INFORMATION

These highlights do not include all the information needed to use MUPIROCIN CREAM safely and effectively. See full prescribing information for MUPIROCIN CREAM.
MUPIROCIN cream, for topical use
Initial U.S. Approval: 1987

1 INDICATIONS AND USAGE

Mupirocin cream is an RNA synthetase inhibitor antibacterial indicated for the treatment of secondarily infected traumatic skin lesions (up to 10 cm in length or 100 cm^2 in area) due to susceptible isolates of Staphylococcus aureus and Streptococcus pyogenes. (1)

2 DOSAGE AND ADMINISTRATION

- For Topical Use Only. (2)
- Apply a small amount of mupirocin cream, with a cotton swab or gauze pad, to the affected area 3 times daily for 10 days. (2)
- Re-evaluate patients not showing a clinical response within 3 to 5 days. (2)
- Not for intranasal, ophthalmic, or other mucosal use. (2)

3 DOSAGE FORMS AND STRENGTHS

Cream: 20 mg (2% w/w) of mupirocin per gram (equivalent to 21.5 mg (2.15% w/w) of mupirocin calcium, USP) in 15-gram and 30-gram tubes. (3)

4 CONTRAINDICATIONS

Known hypersensitivity to mupirocin or any of the excipients of mupirocin cream. (4)

5 WARNINGS AND PRECAUTIONS

- Severe Allergic Reactions: Anaphylaxis, urticaria, angioedema, and generalized rash have been reported in patients treated with formulations of mupirocin, including mupirocin cream. (5.1)
- Eye Irritation: Avoid contact with eyes. (5.2)
- Local Irritation: Discontinue in the event of sensitization or severe local irritation. (5.3)
- Clostridium difficile-Associated Diarrhea (CDAD): If diarrhea occurs, evaluate patients for CDAD. (5.4)
- Potential for Microbial Overgrowth: Prolonged use may result in overgrowth of nonsusceptible microorganisms, including fungi. (5.5)
- Risk Associated with Mucosal Use: Mupirocin cream is not formulated for use on mucosal surfaces. A separate formulation, mupirocin nasal ointment, is available for intranasal use. (5.6)

6 ADVERSE REACTIONS

- The most frequent adverse reactions (at least 1%) were headache, rash, and nausea. (6.1)

To report SUSPECTED ADVERSE REACTIONS, contact Encube Ethicals Private Limited at 1-833-285-4151 or FDA at 1-800-FDA-1088 or www.fda.gov/medwatch.

FULL PRESCRIBING INFORMATION

1 INDICATIONS AND USAGE

Mupirocin Cream USP, 2% is indicated for the treatment of secondarily infected traumatic skin lesions (up to 10 cm in length or 100 cm^2 in area) due to susceptible isolates of Staphylococcus aureus (S. aureus) and Streptococcus pyogenes (S. pyogenes).

2 DOSAGE AND ADMINISTRATION

- For Topical Use Only.
- Apply a small amount of mupirocin cream, with a cotton swab or gauze pad, to the affected area 3 times daily for 10 days.
- Cover the treated area with gauze dressing if desired.
- Re-evaluate patients not showing a clinical response within 3 to 5 days.
- Mupirocin cream is not for intranasal, ophthalmic, or other mucosal use [see Warnings and Precautions (5.2, 5.6)] .
- Do not apply mupirocin cream concurrently with any other lotions, creams, or ointments [see Clinical Pharmacology (12.3)].

3 DOSAGE FORMS AND STRENGTHS

Mupirocin Cream USP, 2% m is a white cream that contains 20 mg (2% w/w) of mupirocin per gram in an oil- and water-based emulsion, supplied in 15-gram and 30-gram tubes.

4 CONTRAINDICATIONS

Mupirocin cream is contraindicated in patients with known hypersensitivity to mupirocin or any of the excipients of mupirocin cream.

5 WARNINGS AND PRECAUTIONS

5.1 Severe Allergic Reactions

Systemic allergic reactions, including anaphylaxis, urticaria, angioedema, and generalized rash, have been reported in patients treated with formulations of mupirocin, including mupirocin cream [see Adverse Reactions (6.2)].

5.2 Eye Irritation

Avoid contact with the eyes. In case of accidental contact, rinse well with water.

5.3 Local Irritation

In the event of a sensitization or severe local irritation from mupirocin cream, usage should be discontinued, and appropriate alternative therapy for the infection instituted.

5.4 Clostridium difficile-Associated Diarrhea

Clostridium difficile-associated diarrhea (CDAD) has been reported with use of nearly all antibacterial agents and may range in severity from mild diarrhea to fatal colitis. Treatment with antibacterial agents alters the normal flora of the colon leading to overgrowth of C. difficile.

C. difficile produces toxins A and B which contribute to the development of CDAD. Hypertoxin-producing strains of C. difficile cause increased morbidity and mortality, as these infections can be refractory to antimicrobial therapy and may require colectomy. CDAD must be considered in all patients who present with diarrhea following antibacterial drug use. Careful medical history is necessary since CDAD has been reported to occur over 2 months after the administration of antibacterial agents.

If CDAD is suspected or confirmed, ongoing antibacterial drug use not directed against C. difficile may need to be discontinued. Appropriate fluid and electrolyte management, protein supplementation, antibacterial treatment of C. difficile, and surgical evaluation should be instituted as clinically indicated.

5.5 Potential for Microbial Overgrowth

As with other antibacterial products, prolonged use of mupirocin cream may result in overgrowth of nonsusceptible microorganisms, including fungi [see Dosage and Administration (2)] .

5.6 Risk Associated with Mucosal Use

Mupirocin cream is not formulated for use on mucosal surfaces. A separate formulation, mupirocin nasal ointment, is available for intranasal use.

6 ADVERSE REACTIONS

The following adverse reactions are discussed in more detail in other sections of the labeling:

- Severe Allergic Reactions [see Warnings and Precautions (5.1)]
- Eye Irritation [see Warnings and Precautions (5.2)]
- Local Irritation [see Warnings and Precautions (5.3)]
- Clostridium difficile-Associated Diarrhea [see Warnings and Precautions (5.4)]

6.1 Clinical Trials Experience

Because clinical trials are conducted under widely varying conditions, adverse reaction rates observed in the clinical trials of a drug cannot be directly compared with rates in the clinical trials of another drug and may not reflect the rates observed in practice.

In 2 randomized, double-blind, double-dummy trials, 339 subjects were treated with topical mupirocin cream plus oral placebo. Adverse reactions occurred in 28 (8.3%) subjects. The following adverse reactions were reported by at least 1% of subjects in connection with the use of mupirocin cream in clinical trials: headache (1.7%), rash (1.1%), and nausea (1.1%).

Other adverse reactions which occurred in less than 1% of subjects were: abdominal pain, burning at application site, cellulitis, dermatitis, dizziness, pruritus, secondary wound infection, and ulcerative stomatitis.

In a supportive trial in the treatment of secondarily infected eczema, 82 subjects were treated with mupirocin cream. The incidence of adverse reactions was as follows: nausea (4.9%), headache and burning at application site (3.6% each), pruritus (2.4%), and 1 report each of abdominal pain, bleeding secondary to eczema, pain secondary to eczema, hives, dry skin, and rash.

6.2 Postmarketing Experience

In addition to adverse reactions reported from clinical trials, the following reactions have been identified during postmarketing use of mupirocin cream. Because they are reported voluntarily from a population of unknown size, estimates of frequency cannot be made. These reactions have been chosen for inclusion due to a combination of their seriousness, frequency of reporting, or potential causal relationship to mupirocin cream.

Immune System Disorders

Systemic allergic reactions, including anaphylaxis, urticaria, angioedema, and generalized rash [see Warnings and Precautions (5.1)] .

8 USE IN SPECIFIC POPULATIONS

8.1 Pregnancy

Risk Summary

There are insufficient human data to establish whether there is a drug-associated risk with mupirocin cream in pregnant women. Systemic absorption of mupirocin through intact human skin is minimal following topical administration of mupirocin cream [see Clinical Pharmacology (12.3)] . No developmental toxicity was observed in rats or rabbits treated with mupirocin subcutaneously during organogenesis at doses of 160 or 40 mg per kg per day, respectively (22 and 11 times the human topical dose based on calculations of dose divided by the entire body surface area).

The estimated background risk of major birth defects and miscarriage for the indicated population is unknown. The estimated background risk in the U.S. general population of major birth defects is 2% to 4% and of miscarriage is 15% to 20% of clinically recognized pregnancies.

Data

Animal Data: Developmental toxicity studies have been performed with mupirocin administered subcutaneously to rats and rabbits at doses up to 160 mg per kg per day during organogenesis. This dose is 22 and 43 times, respectively, the human topical dose (approximately 60 mg mupirocin per day) based on calculations of dose divided by the entire body surface area. Maternal toxicity was observed (body weight loss/decreased body weight gain and reduced feeding) in both species with no evidence of developmental toxicity in rats. In rabbits, excessive maternal toxicity at the high dose precluded the evaluation of fetal outcomes. There was no developmental toxicity in rabbits at 40 mg per kg per day, 11 times the human topical dose based on calculations of dose divided by the entire body surface area.

Mupirocin administered subcutaneously to rats in a pre- and postnatal development study (dosed during late gestation through lactation) was associated with reduced offspring viability in the early postnatal period at a dose of 106.7 mg per kg, in the presence of injection site irritation and/or subcutaneous hemorrhaging. This dose is 14 times the human topical dose based on calculations of dose divided by the entire body surface area. The no-observed adverse effect level in this study was 44.2 mg per kg per day, which is 6 times the human topical dose.

8.2 Lactation

Risk Summary

It is not known whether mupirocin is present in human milk, has effects on the breastfed child, or has effects on milk production. However, breastfeeding is not expected to result in exposure of the child to the drug due to the minimal systemic absorption of mupirocin in humans following topical administration of mupirocin cream [see Clinical Pharmacology (12.3)] . The developmental and health benefits of breastfeeding should be considered along with the mother’s clinical need for mupirocin cream and any potential adverse effects on the breastfed child from mupirocin cream or from the underlying maternal condition.

Clinical Considerations

To minimize oral exposure of the drug to children, a breast and/or nipple being treated with mupirocin cream should be thoroughly washed prior to breastfeeding.

8.4 Pediatric Use

The safety and effectiveness of mupirocin cream have been established in the age-groups of 3 months to 16 years. Use of mupirocin cream in these age-groups is supported by evidence from adequate and well-controlled trials of mupirocin cream in adults with additional data from 93 pediatric subjects studied as part of the pivotal trials in adults [see Clinical Studies (14)] .

8.5 Geriatric Use

In 2 adequate and well-controlled trials, 30 subjects older than 65 years were treated with mupirocin cream. No overall difference in the efficacy or safety of mupirocin cream was observed in this patient population when compared with that observed in younger patients.

11 DESCRIPTION

Mupirocin Cream USP, 2% contains the dihydrate crystalline calcium hemi-salt of the RNA synthetase inhibitor antibacterial, mupirocin. Chemically, it is (α E,2 S,3 R,4 R,5 S)-5-[(2 S,3 S,4 S,5 S)-2,3-epoxy-5-hydroxy-4-methylhexyl]tetrahydro-3,4-dihydroxy-β-methyl-2 H-pyran-2-crotonic acid, ester with 9-hydroxynonanoic acid, calcium salt (2:1), dihydrate.

The molecular formula of mupirocin calcium, USP is (C26H43O9)2Ca•2H2O, and the molecular weight is 1075.3 g/mol. The molecular weight of mupirocin free acid is 500.6 g/mol. The structural formula of mupirocin calcium, USP is:

Each gram of mupirocin cream contains 20 mg (2% w/w) of mupirocin equivalent to 21.5 mg (2.15% w/w) of mupirocin calcium. The inactive ingredients are benzyl alcohol, polyoxyl 20 cetostearyl ether, mono and di-glycerides, mineral oil, phenoxyethanol, purified water and xanthan gum.

12 CLINICAL PHARMACOLOGY

12.1 Mechanism of Action

Mupirocin is an RNA synthetase inhibitor antibacterial [see Microbiology (12.4)].

12.3 Pharmacokinetics

Absorption

Systemic absorption of mupirocin through intact human skin is minimal. The systemic absorption of mupirocin was studied following application of mupirocin cream 3 times daily for 5 days to various skin lesions greater than 10 cm in length or 100 cm^2 in area in 16 adults (aged 29 to 60 years) and 10 children (aged 3 to 12 years). Some systemic absorption was observed as evidenced by the detection of the metabolite, monic acid, in urine. Data from this trial indicated more frequent occurrence of percutaneous absorption in children (90% of subjects) compared with adults (44% of subjects); however, the observed urinary concentrations in children (0.07 to 1.3 mcg per mL [1 pediatric subject had no detectable level]) are within the observed range (0.08 to 10.03 mcg per mL [9 adults had no detectable level]) in the adult population. In general, the degree of percutaneous absorption following multiple dosing appears to be minimal in adults and children.

The effect of the concurrent application of mupirocin cream with other topical products has not been studied [see Dosage and Administration (2)] .

Elimination

In a trial conducted in 7 healthy adult male subjects, the elimination half-life after intravenous administration of mupirocin was 20 to 40 minutes for mupirocin and 30 to 80 minutes for monic acid.

Metabolism: Following intravenous or oral administration, mupirocin is rapidly metabolized. The principal metabolite, monic acid, demonstrates no antibacterial activity.

Excretion: Monic acid is predominantly eliminated by renal excretion.

12.4 Microbiology

Mupirocin is an RNA synthetase inhibitor antibacterial produced by fermentation using the organism Pseudomonas fluorescens.

Mechanism of Action

Mupirocin inhibits bacterial protein synthesis by reversibly and specifically binding to bacterial isoleucyl-transfer RNA (tRNA) synthetase.

Mupirocin is bactericidal at concentrations achieved by topical administration. Mupirocin is highly protein bound (greater than 97%) and the effect of wound secretions on the minimum inhibitory concentrations (MICs) of mupirocin has not been determined.

Resistance

When mupirocin resistance occurs, it results from the production of a modified isoleucyl-tRNA synthetase, or the acquisition of, by genetic transfer, a plasmid mediating a new isoleucyl-tRNA synthetase. High-level plasmid-mediated resistance (MIC ≥512 mcg/mL) has been reported in increasing numbers of isolates of S. aureus and with higher frequency in coagulase-negative staphylococci. Mupirocin resistance occurs with greater frequency in methicillin-resistant than methicillin-susceptible staphylococci.

Cross Resistance

Due to its mode of action, mupirocin does not demonstrate cross resistance with other classes of antimicrobial agents.

Antimicrobial Activity

Mupirocin has been shown to be active against susceptible isolates of S. aureus and S. pyogenes, both in vitro and in clinical trials [see Indications and Usage (1)]. The following in vitro data are available, but their clinical significance is unknown. Mupirocin is active against most isolates of Staphylococcus epidermidis.

Susceptibility Test Methods

High-level mupirocin resistance (≥512 mcg/mL) may be determined using standard disk diffusion or broth microdilution tests.^1,2 Because of the occurrence of mupirocin resistance in methicillin-resistant S. aureus (MRSA), it is appropriate to test MRSA populations for mupirocin susceptibility prior to the use of mupirocin using a standardized method. ^3,4,5

13 NONCLINICAL TOXICOLOGY

13.1 Carcinogenesis, Mutagenesis, Impairment of Fertility

Long-term studies in animals to evaluate carcinogenic potential of mupirocin calcium have not been conducted.

Results of the following studies performed with mupirocin calcium or mupirocin sodium in vitro and in vivo did not indicate a potential for genotoxicity: rat primary hepatocyte unscheduled DNA synthesis, sediment analysis for DNA strand breaks, Salmonella reversion test (Ames), Escherichia coli mutation assay, metaphase analysis of human lymphocytes, mouse lymphoma assay, and bone marrow micronuclei assay in mice.

In a fertility/reproductive performance study (with dosing through lactation), mupirocin administered subcutaneously to male and female rats at doses up to 100 mg per kg per day which is 14 times the human topical dose (approximately 60 mg mupirocin per day) based on calculations of dose divided by the entire body surface area, did not result in impaired fertility or impaired reproductive performance attributable to mupirocin.

14 CLINICAL STUDIES

The efficacy of topical mupirocin cream for the treatment of secondarily infected traumatic skin lesions (e.g., lacerations, sutured wounds, and abrasions not more than 10 cm in length or 100 cm^2 in total area) was compared with that of oral cephalexin in 2 randomized, double-blind, double-dummy clinical trials. Clinical efficacy rates at follow-up in the per-protocol populations (adults and pediatric subjects included) were 96.1% for mupirocin cream (n = 231) and 93.1% for oral cephalexin (n = 219). Pathogen eradication rates at follow-up in the per-protocol populations were 100% for both mupirocin cream and oral cephalexin.

Pediatrics

There were 93 pediatric subjects aged 2 weeks to 16 years enrolled per protocol in the secondarily infected skin lesion trials, although only 3 were younger than 2 years of age in the population treated with mupirocin cream. Subjects were randomized to either 10 days of topical mupirocin cream 3 times daily or 10 days of oral cephalexin (250 mg 4 times daily for subjects greater than 40 kg or 25 mg per kg per day oral suspension in 4 divided doses for subjects less than or equal to 40 kg). Clinical efficacy at follow-up (7 to 12 days post-therapy) in the per-protocol populations was 97.7% (43 of 44) for mupirocin cream and 93.9% (46 of 49) for cephalexin.

15 REFERENCES

1. Clinical and Laboratory Standards Institute (CLSI). Performance Standards for Antimicrobial Susceptibility Testing; Twenty-sixth Informational Supplement. CLSI document M100-S26. Clinical and Laboratory Standards Institute, 950 West Valley Rd., Suite 2500, Wayne, PA 19087, USA, 2016.

2. Patel J, Gorwitz RJ, et al. Mupirocin Resistance. Clinical Infectious Diseases. 2009; 49(6): 935-41.

3. Clinical and Laboratory Standards Institute (CLSI). Methods for Dilution Antimicrobial Susceptibility Tests for Bacteria that Grow Aerobically; Approved Standard – Tenth Edition . CLSI document M07-A10. Clinical and Laboratory Standards Institute, 950 West Valley Road, Suite 2500, Wayne, Pennsylvania 19087, USA, 2015.

4. Clinical and Laboratory Standards Institute (CLSI). Performance Standards for Antimicrobial Disk Diffusion Susceptibility Tests; Approved Standard – Twelfth Edition. CLSI document M02-A12. Clinical and Laboratory Standards Institute, 950 West Valley Road, Suite 2500, Wayne, Pennsylvania 19087, USA, 2015.

5. Finlay JE, Miller LA, Poupard JA. Interpretive criteria for testing susceptibility of staphylococci to mupirocin. Antimicrob Agents Chemother. 1997; 41(5):1137-1139.

16 HOW SUPPLIED/STORAGE AND HANDLING

Mupirocin Cream USP, 2% is a white cream that contains 20 mg (2% w/w) of mupirocin per gram in an oil- and water-based emulsion.

Mupirocin Cream USP, 2% is supplied in 15-gram and 30-gram tubes.

NDC 21922-029-04 (15-gram tube)
NDC 21922-029-05 (30-gram tube)

Store at 20°C to 25°C (68°F to 77°F) [see USP Controlled Room Temperature]. Do not freeze.

17 PATIENT COUNSELING INFORMATION

dvise the patient to read the FDA-approved patient labeling (Patient Information).

Advise the patient to administer mupirocin cream as follows:

Use mupirocin cream only as directed by the healthcare provider. It is for external use only. Avoid contact of mupirocin cream with the eyes. If mupirocin cream gets in the eyes, rinse thoroughly with water.

- Do not use mupirocin cream in the nose.
- Wash your hands before and after applying mupirocin cream.
- Use a gauze pad or cotton swab to apply a small amount of mupirocin cream to the affected area. The treated area may be covered by gauze dressing if desired.
- Report to the healthcare provider any signs of local adverse reactions. Mupirocin cream should be stopped and the healthcare provider contacted if irritation, severe itching, or rash occurs.
- Report to the healthcare provider or go to the nearest emergency room if severe allergic reactions, such as swelling of the lips, face, or tongue, or wheezing occur [see Warnings and Precautions (5.1)] .
- If no improvement is seen in 3 to 5 days, contact the healthcare provider.

Manufactured by:

Encube Ethicals Private Limited
Plot No. C-1, Madkaim Industrial Estate,
Madkaim, Post: Mardol, Ponda,
Goa - 403 404, India.

Distributed by:
Encube Ethicals, Inc.
200 Meredith Avenue, Suite 101A
Durham, NC 27713 USA

Rev. 11/2021

PHARMACIST-DETACH HERE AND GIVE INSTRUCTIONS TO PATIENT

---------------------------------------------------------------------------------------------------------------------------------------------------------------

Patient Information

MUPIROCIN (mue pir'oh sin)
CREAM, for topical use

What is mupirocin cream?

Mupirocin cream is a prescription medicine used on the skin (topical use) to treat certain skin infections caused by bacteria called Staphylococcus aureus and Streptococcus pyogenes. It is not known if mupirocin cream is safe and effective in children under 3 months of age.

Who should not use mupirocin cream?

Do not use mupirocin cream if:

- you are allergic to mupirocin or any of the ingredients in mupirocin cream. See the end of this Patient Information leaflet for a complete list of the ingredients in mupirocin cream.

What should I tell my healthcare provider before using mupirocin cream?

Before using mupirocin cream, tell your healthcare provider about all of your medical conditions including if you:

- are pregnant or plan to become pregnant. It is not known if mupirocin cream will harm your unborn baby.•are breastfeeding or plan to breastfeed. It is not known if mupirocin passes into your breast milk. You and your healthcare provider should decide if you can use mupirocin cream while breastfeeding.

Tell your healthcare provider about all of the medicines you take, including prescription and over-the-counter medicines, vitamins, and herbal supplements. Do not mix mupirocin cream with other lotions, creams, or ointments.

How should I use mupirocin cream?

- Mupirocin cream is for use on the skin (topical). Do not get mupirocin cream in your eyes, nose, mouth, or vagina (mucosal surfaces).
- Use mupirocin cream exactly as your healthcare provider tells you to use it.
- Apply a small amount of mupirocin cream, with a cotton swab or gauze pad, to the affected area 3 times each day. Apply mupirocin cream for 10 days.
- It is important that you take the full course of mupirocin cream. Do not stop early because your symptoms may disappear before the infection is fully cleared.
- Wash your hands before and after applying mupirocin cream.
- After applying mupirocin cream, you may cover the treated area with a clean gauze pad, unless your healthcare provider has told you to leave it uncovered.
- Talk to your healthcare provider if your skin does not improve after 3 to 5 days of treatment with mupirocin cream.
- If you are breastfeeding and use mupirocin cream on your breast or nipple, wash the area well before breastfeeding your child.

What are the possible side effects of mupirocin cream?

Mupirocin cream may cause serious side effects, including:

- severe allergic reactions. Stop using mupirocin cream and call your healthcare provider or go to the nearest emergency room right away if you have any of the following signs or symptoms of a severe allergic reaction:

- hives

- trouble breathing or wheezing

- swelling of your face, lips, mouth, or tongue

- dizziness, fast heartbeat, or pounding in your chest

- a rash over your whole body

- eye irritation. Do not get mupirocin cream in your eyes. If mupirocin cream gets in your eyes, rinse your eyes well with water .
- irritation in the area mupirocin cream is used. A rash may occur after using mupirocin cream and can be severe. Stop using mupirocin cream and call your healthcare provider if you develop an irritation, severe itching, or a rash while using mupirocin cream.
- a type of diarrhea called clostridium difficile-associated diarrhea (CDAD). CDAD may happen in people who use or have used medicine to treat bacterial infections. The severity of CDAD can range from mild diarrhea to severe diarrhea that may cause death (fatal colitis). Call your healthcare provider or go to the nearest emergency room right away if you have diarrhea while using or after you stop using mupirocin cream.

The most common side effects of mupirocin cream include:

- headache
- rash
- nausea

These are not all the possible side effects of mupirocin cream. Call your doctor for medical advice about side effects. You may report side effects to FDA at 1-800-FDA-1088.

How should I store mupirocin cream?

- Store mupirocin cream at room temperature between 68°F to 77°F (20°C to 25°C).
- Do not freeze mupirocin cream.
- Keep mupirocin cream and all medicines out of the reach of children.

General information about the safe and effective use of mupirocin cream.

Medicines are sometimes prescribed for purposes other than those listed in a Patient Information leaflet. Do not use mupirocin cream for a condition for which it was not prescribed. Do not give mupirocin cream to other people, even if they have the same symptoms that you have. It may harm them. You can ask your pharmacist or healthcare provider for information about mupirocin cream that is written for health professionals.

What are the ingredients in mupirocin cream?

Active Ingredient: mupirocin calcium

Inactive Ingredients: benzyl alcohol, polyoxyl 20 cetostearyl ether, mono- and di-glycerides, mineral oil, phenoxyethanol, purified water and xanthan gum.

Manufactured by:
Encube Ethicals Private Limited
Plot No. C-1, Madkaim Industrial Estate,
Madkaim, Post: Mardol, Ponda,
Goa - 403 404, India.

Distributed by:
Encube Ethicals, Inc.
200 Meredith Avenue, Suite 101A
Durham, NC 27713 USA
This Patient Information has been approved by the U.S. Food and Drug Administration Revised: 11/2021

PACKAGE/LABEL PRINCIPAL DISPLAY PANEL

Tube Label

NDC 21922-029-04 (Mupirocin Cream USP, 2% - Tube-15 g)

NDC 21922-029-04

Mupirocin Cream USP, 2%

For topical use

15 g (Net Wt.)

Rx only

Carton Label

NDC 21922-029-04 (Mupirocin Cream USP, 2% - Tube-15 g)

NDC 21922-029-04

Mupirocin Cream USP, 2%

For topical use

15 g (Net Wt.)

Rx only

PACKAGE/LABEL PRINCIPAL DISPLAY PANEL

ube Label

NDC 21922-029-05 (Mupirocin Cream USP, 2% - Tube-30 g)

NDC 21922-029-05

Mupirocin Cream USP, 2%

For topical use

30 g (Net Wt.)

Rx only

Carton Label

NDC 21922-029-05 (Mupirocin Cream USP, 2% - Tube-30 g)

NDC 21922-029-05

Mupirocin Cream USP, 2%

For topical use

30 g (Net Wt.)

Rx only